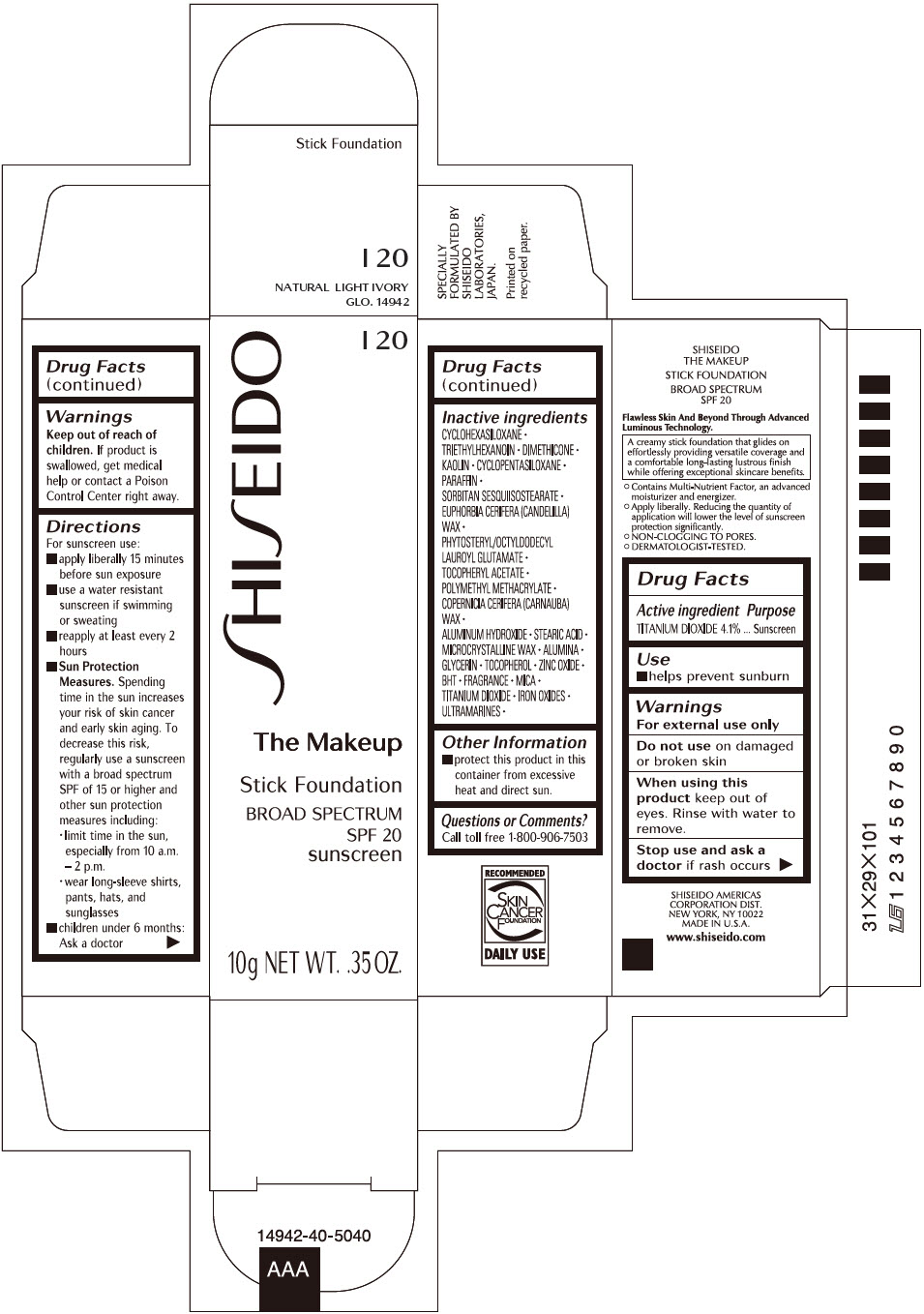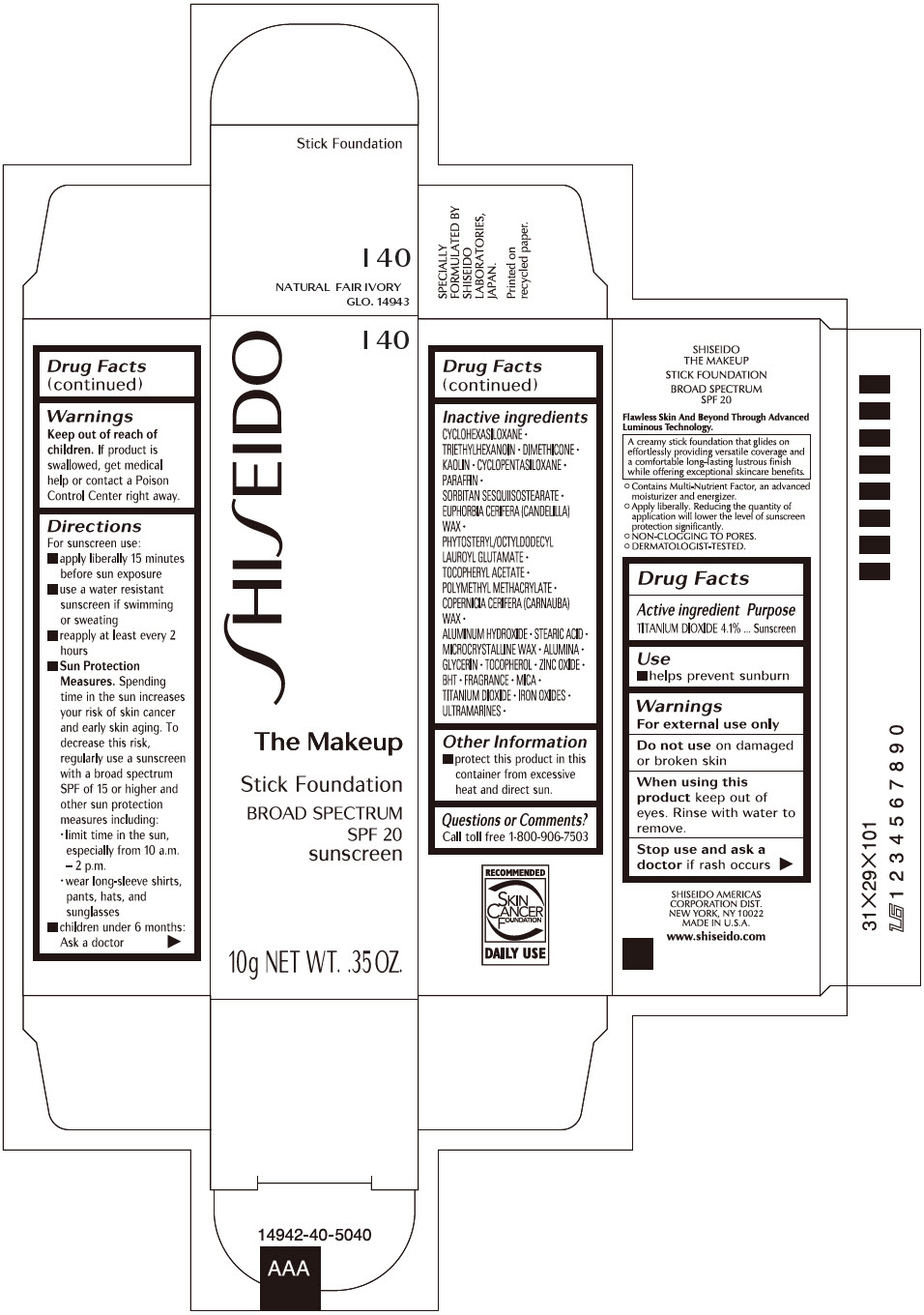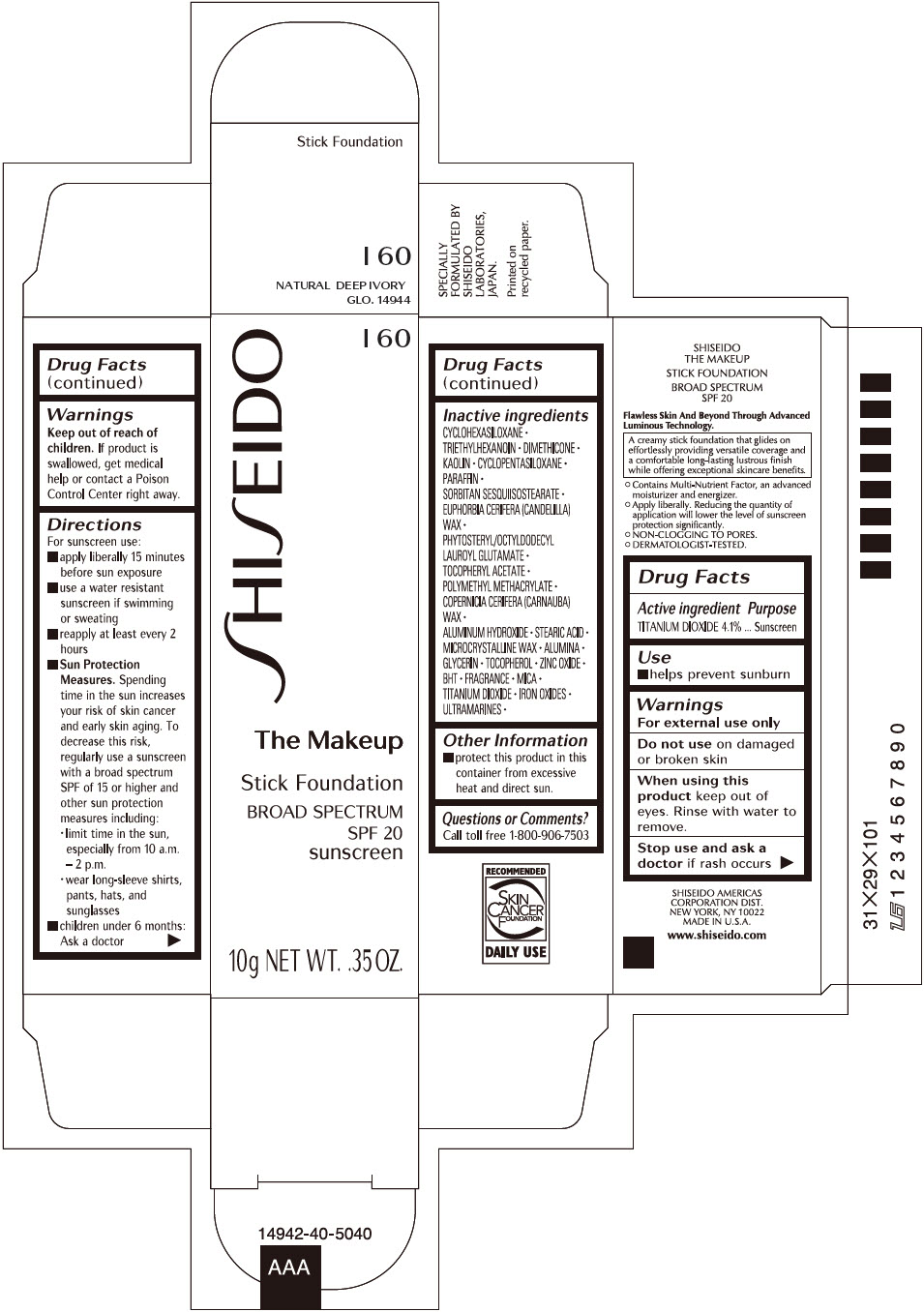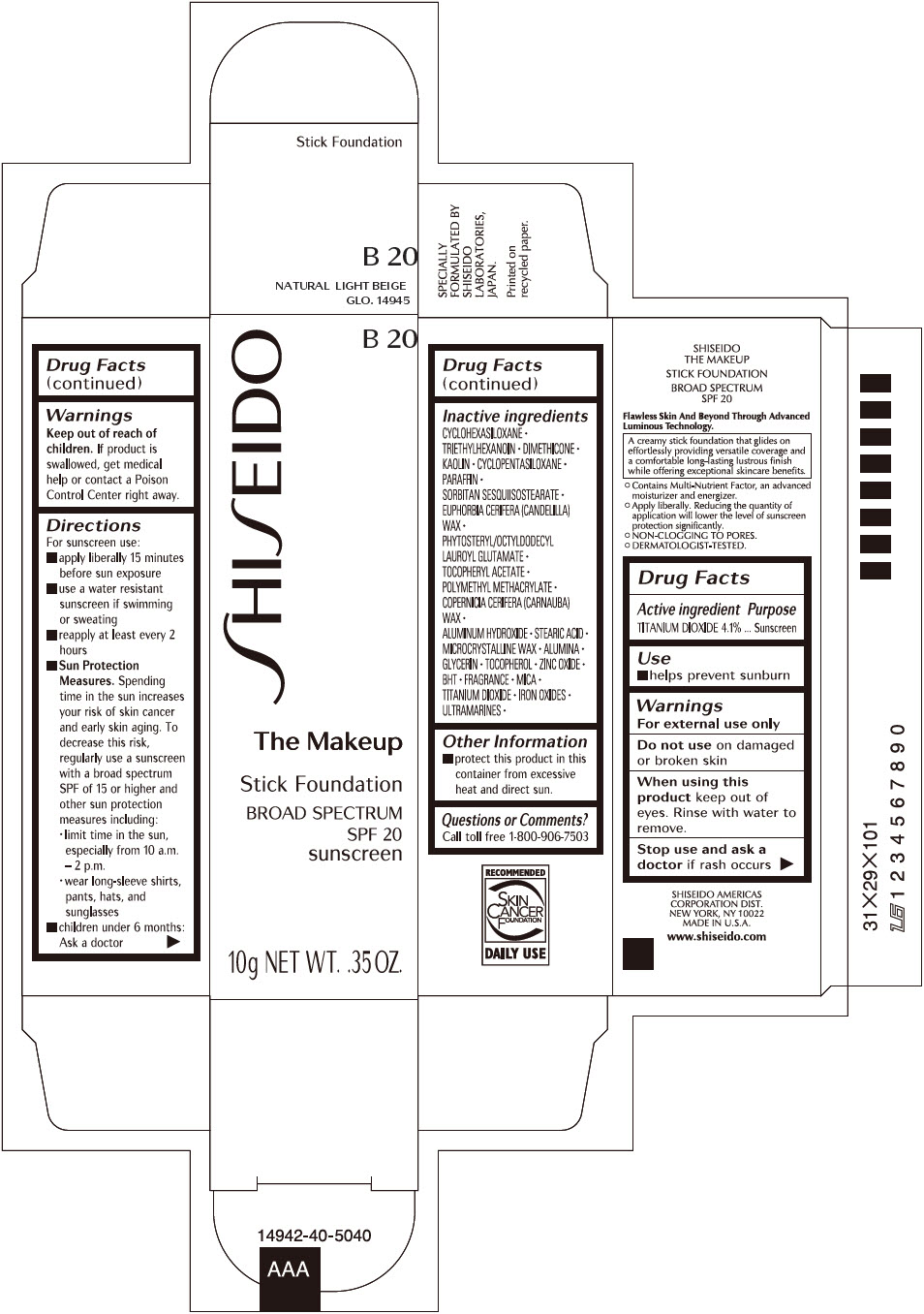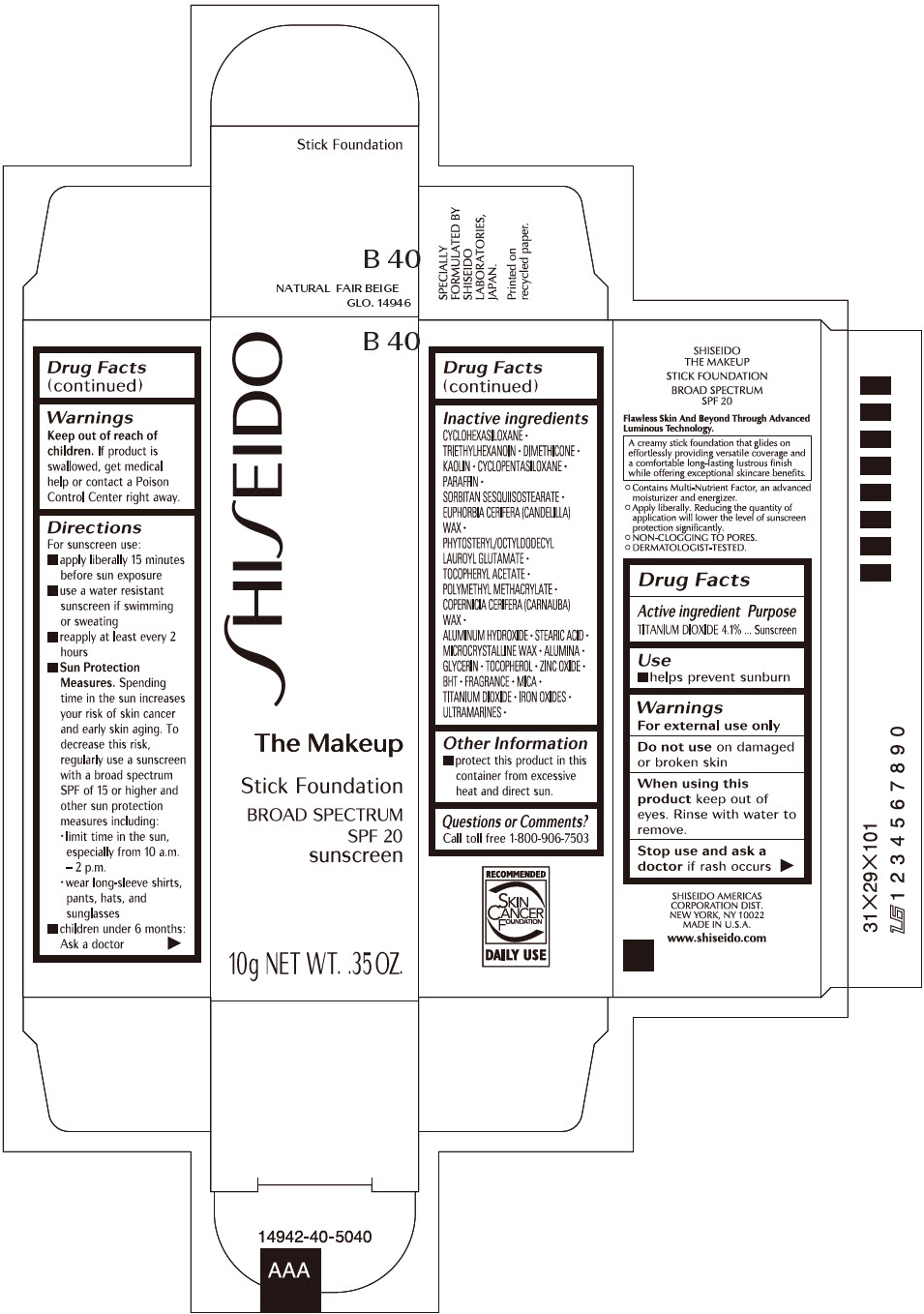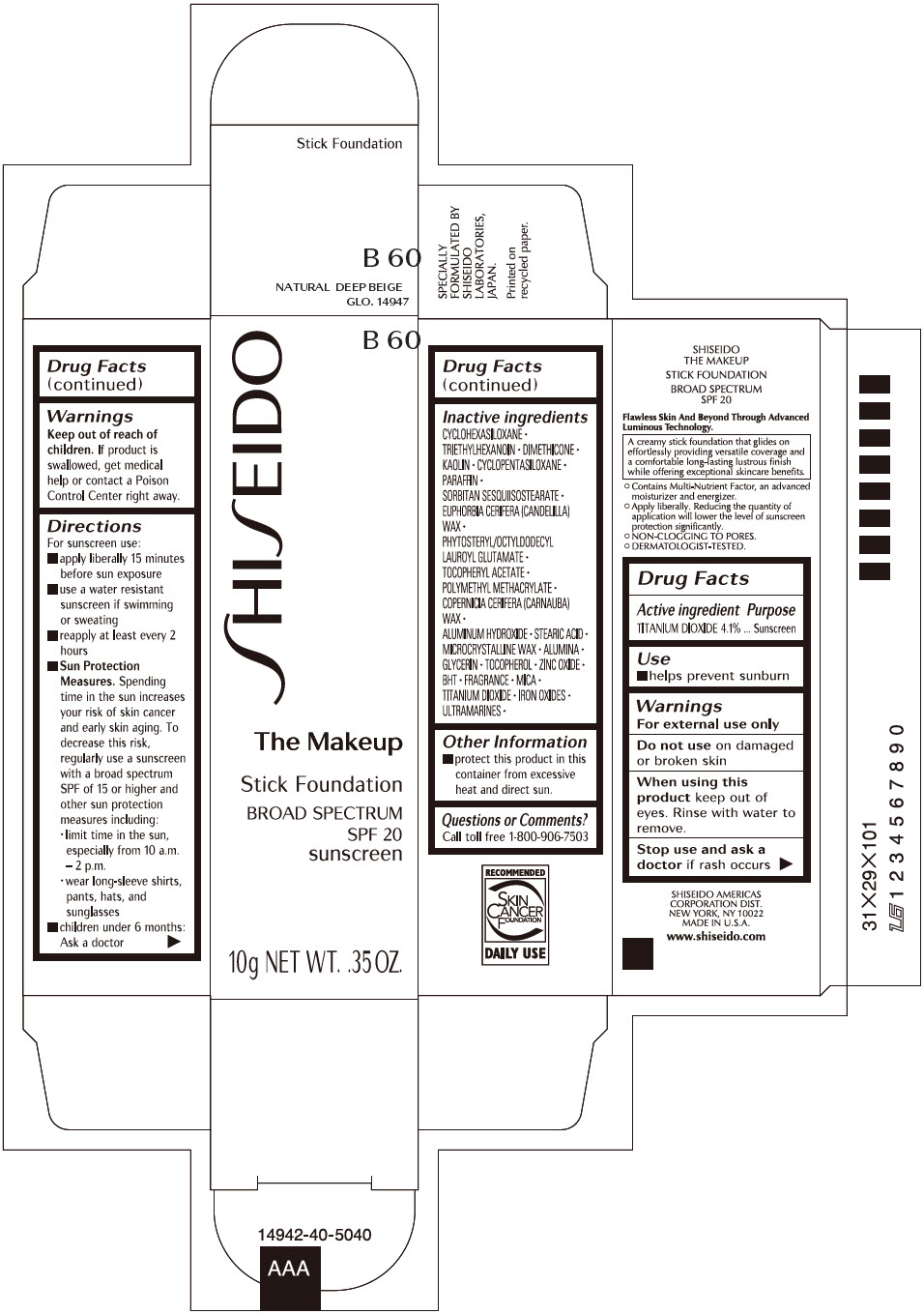 DRUG LABEL: SHISEIDO THE MAKEUP FOUNDATION

NDC: 58411-458 | Form: STICK
Manufacturer: SHISEIDO AMERICAS CORPORATION
Category: otc | Type: HUMAN OTC DRUG LABEL
Date: 20260105

ACTIVE INGREDIENTS: TITANIUM DIOXIDE 400 mg/10 g
INACTIVE INGREDIENTS: CYCLOMETHICONE 6; TRIETHYLHEXANOIN; DIMETHICONE; KAOLIN; CYCLOMETHICONE 5; PARAFFIN; SORBITAN SESQUIISOSTEARATE; CANDELILLA WAX; PHYTOSTERYL/OCTYLDODECYL LAUROYL GLUTAMATE; .ALPHA.-TOCOPHEROL ACETATE, DL-; POLY(METHYL METHACRYLATE; 450000 MW); CARNAUBA WAX; ALUMINUM HYDROXIDE; STEARIC ACID; MICROCRYSTALLINE WAX; ALUMINUM OXIDE; GLYCERIN; .ALPHA.-TOCOPHEROL; ZINC OXIDE; BUTYLATED HYDROXYTOLUENE; MICA; FERRIC OXIDE RED; FERRIC OXIDE YELLOW; FERROSOFERRIC OXIDE

SHISEIDO THE MAKEUP STICK FOUNDATION

Drug Facts

Active ingredients

Titanium Dioxide 4.1%

Purpose

Sunscreen

Uses

- helps prevent sunburn

Warnings

For external use only

Do not use on damaged or broken skin

WHEN USING

When using this productkeep out of eyes. Rinse with water to remove.

Stop use and ask a doctorif rash occurs.

Keep out of reach of children.If product is swallowed, get medical help or contact a Poison Control Center right away.

Directions

For sunscreen use:

- apply liberally 15 minutes before sun exposure
- use a water resistant sunscreen if swimming or sweating
- reapply at least every 2 hours
- children under 6 months: ask a doctor
- Sun Protection Measures. Spending time in the sun increases your risk of skin cancer and early skin aging. To decrease this risk, regularly use a sunscreen with a broad spectrum SPF of 15 or higher and other sun protection measures including:
  - limit time in the sun, especially from 10 a.m. – 2 p.m.
  - wear long-sleeve shirts, pants, hats, and sunglasses
- Children under 6 months: Ask a doctor

Inactive Ingredients

CYCLOHEXASILOXANE ∙ TRIETHYLHEXANOIN ∙ DIMETHICONE ∙ KAOLIN ∙ CYCLOPENTASILOXANE ∙ PARAFFIN ∙ SORBITAN SESQUIISOSTEARATE ∙ EUPHORBIA CERIFERA (CANDELILLA) WAX ∙ PHYTOSTERYL/OCTYLDODECYL LAUROYL GLUTAMATE ∙ TOCOPHERYL ACETATE ∙ POLYMETHYL METHACRYLATE ∙ COPERNICIA CERIFERA (CARNAUBA) WAX ∙ ALUMINUM HYDROXIDE ∙ STEARIC ACID ∙ MICROCRYSTALLINE WAX ∙ ALUMINA ∙ GLYCERIN ∙ TOCOPHEROL ∙ ZINC OXIDE ∙ BHT ∙ FRAGRANCE ∙ MICA ∙ TITANIUM DIOXIDE ∙ IRON OXIDES ∙ ULTRAMARINES ∙

Other information

Protect this product in this container from excessive heat and direct sun.

Questions or comments?

Call toll free 1-800-906-7503

PRINCIPAL DISPLAY PANEL - 10 g Cartridge Carton - I 20

I 20

SHISEIDO

The Makeup

Stick Foundation
BROAD SPECTRUM
SPF 20
sunscreen

10g NET WT. .35 OZ.

PRINCIPAL DISPLAY PANEL - 10 g Cartridge Carton - I 40

I 40

SHISEIDO

The Makeup

Stick Foundation
BROAD SPECTRUM
SPF 20
sunscreen

10g NET WT. .35 OZ.

PRINCIPAL DISPLAY PANEL - 10 g Cartridge Carton - I 60

I 60

SHISEIDO

The Makeup

Stick Foundation
BROAD SPECTRUM
SPF 20
sunscreen

10g NET WT. .35 OZ.

PRINCIPAL DISPLAY PANEL - 10 g Cartridge Carton - B 20

B 20

SHISEIDO

The Makeup

Stick Foundation
BROAD SPECTRUM
SPF 20
sunscreen

10g NET WT. .35 OZ.

PRINCIPAL DISPLAY PANEL - 10 g Cartridge Carton - B 40

B 40

SHISEIDO

The Makeup

Stick Foundation
BROAD SPECTRUM
SPF 20
sunscreen

10g NET WT. .35 OZ.

PRINCIPAL DISPLAY PANEL - 10 g Cartridge Carton - B 60

B 60

SHISEIDO

The Makeup

Stick Foundation
BROAD SPECTRUM
SPF 20
sunscreen

10g NET WT. .35 OZ.